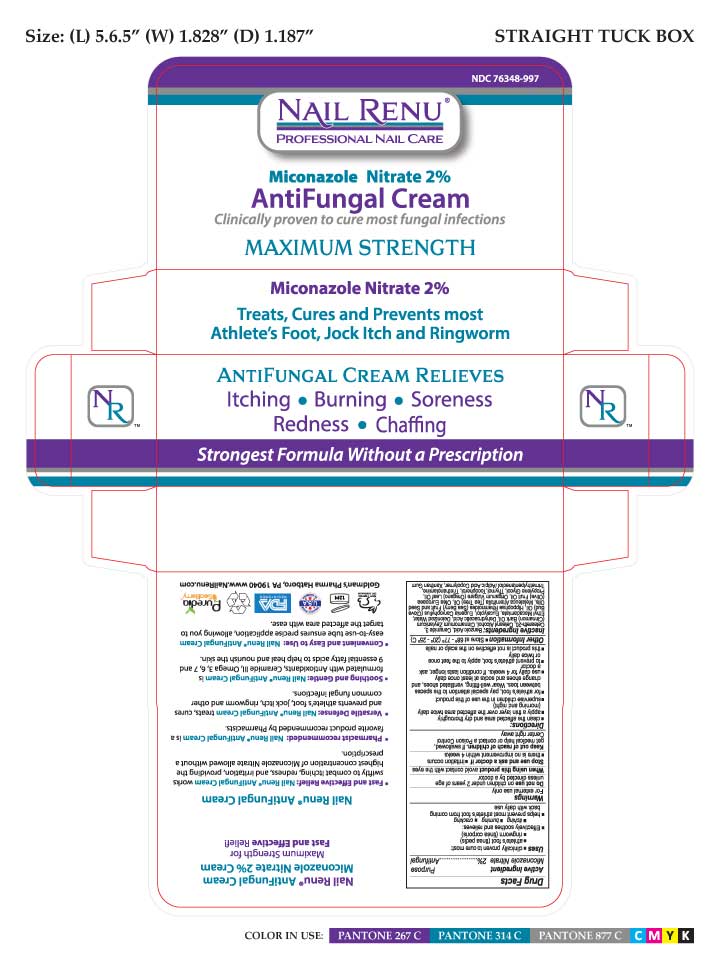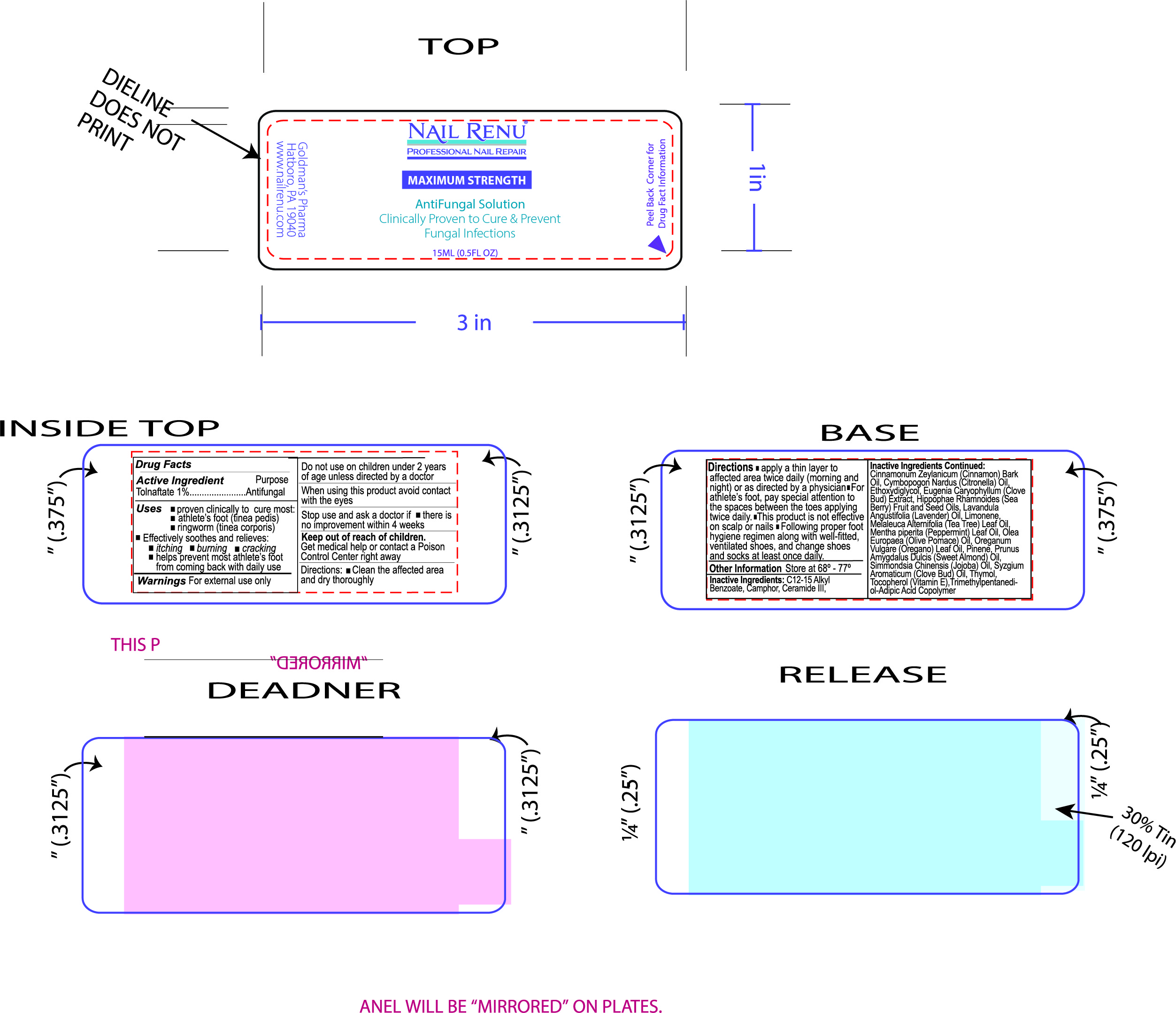 DRUG LABEL: NAIL RENU Antifungal
NDC: 76348-997 | Form: CREAM
Manufacturer: RENU LABORATORIES, INC.
Category: otc | Type: HUMAN OTC DRUG LABEL
Date: 20230724

ACTIVE INGREDIENTS: MICONAZOLE NITRATE 0.6 g/28 g
INACTIVE INGREDIENTS: POLYOXYL 20 CETOSTEARYL ETHER; WATER; EUCALYPTOL; CLOVE OIL; HIPPOPHAE RHAMNOIDES SEED OIL; MELALEUCA ALTERNIFOLIA (TEA TREE) LEAF OIL; OREGANO LEAF OIL; HIPPOPHAE RHAMNOIDES FRUIT OIL; PROPYLENE GLYCOL; THYMOL; TOCOPHEROL; XANTHAN GUM; OLIVE OIL; BENZOIC ACID; CETOSTEARYL ALCOHOL; CINNAMON BARK OIL; DEHYDROACETIC ACID; ETHYL MACADAMIATE; CERAMIDE 3; TROLAMINE; TRIMETHYLPENTANEDIOL/ADIPIC ACID/GLYCERIN CROSSPOLYMER (25000 MPA.S)

NAIL RENU ANTIFUNGAL CREAM

ACTIVE INGREDIENT

Miconazole Nitrate 2%

PURPOSE

Antifungal

Uses

- proven clinically to cure most:
- athlete's foot (tinea pedis)
- ringworm (tinea corporis)
- Effectively soothes and relieves:
- itching
- burning
- cracking
- helps prevent most athlete's foot from coming back, with daily use

RECENT MAJOR CHANGES

There are no major changes. This is a new submission.

WARNINGS

For external use only

When using this product, avoid contact with the eyes

Stop use and ask a doctor if

- irritation occurs
- there is no improvement within 4 weeks

Keep out of reach of children.

If swallowed, get medical help or contact a Poison Control Center right away.

Directions:

- clean the affected area and dry thoroughly
- apply a thin layer over the affected area twice daily (morning and night)
- supervise children in the use of this product
- for athlete's foot, pay special attention to the spaces between toes. Wear well-fitting, ventilated shoes, and change shoes and socks at least once daily
- use daily for 4 weeks, if condition lasts longer, ask a doctor
- to prevent athlete's foot, apply to the feet once or twice daily
- this product is not effective on the scalp or nails

INACTIVE INGREDIENT

Benxoic Acid, Ceramide-3, Ceteareth-20, Cetearyl Alcohol, Cinnamomum Zeylanicum (Cinnamon) Bark Oil, Dehydroacetic Acid, Deionized Water, Ethyl Macadamiate, Eucalyptol, Eugenia Caryophyllus (Clove) Bud Oil, Hippophae Rhamnoides (Sea Berry) Fruit and Seed Oils, Melaleuca Alternifolia (Tea Tree) Oil, Olea Europaea (Olive) Fruit Oil, Origanum vulgare (Oregano) Leaf Oil, Propylene Glycol, Thymol, Tocopherol, Triethanolamine, Trimethylpentanediol Adipic Acid Copolymer, Xanthan Gum

Do not use on Children under 2 years of age unless directed by a doctor.

Other Information

Store at 68º - 77º (20 - 25 C)

STATEMENT OF IDENTITY

NAIL RENU

Miconazole Nitrate 2%

Antifungal Cream

Directions

- Clean the affected area and dry thoroughly
- apply a thin coat over affected area twice daily (morning and night)
- supervise children in the use of this product
- for athlete's foot, pay special attention to the spaces between toes. Wear well-fitting, ventilated shoes, change shoes and socks daily
- use daily for 4 weeks. If condition lasts longer, ask a doctor
- to prevent athlete's foot, apply to the feet once or twice daily
- this product is not effective on the scalp or nails

PACKAGE LABEL

TTUBE ARTWORK AND UNIT BOX ARTWORK FOR NAIL RENU